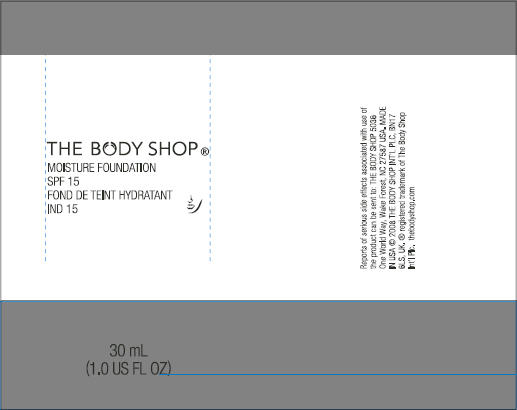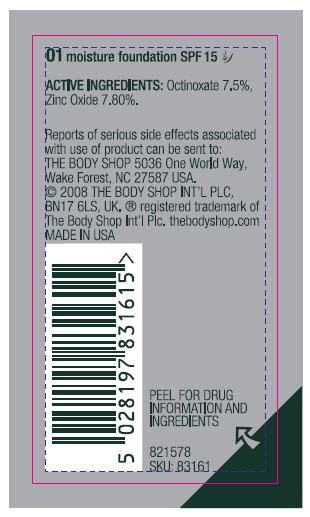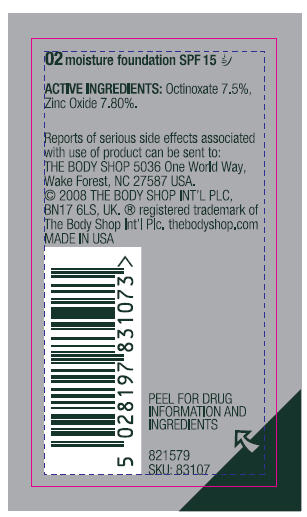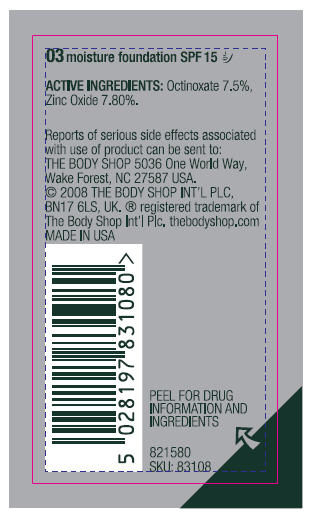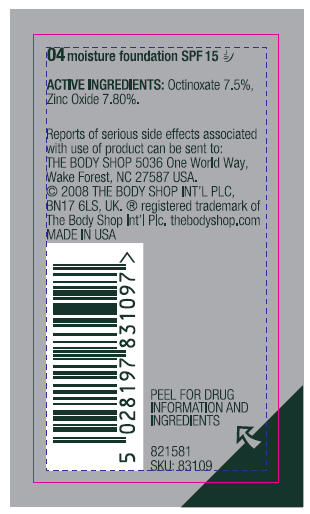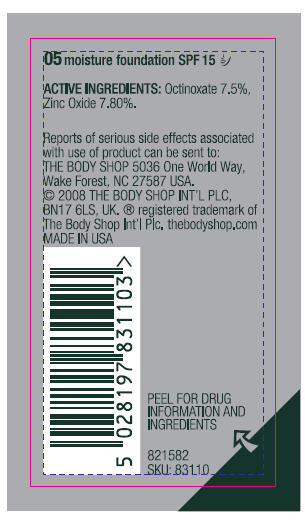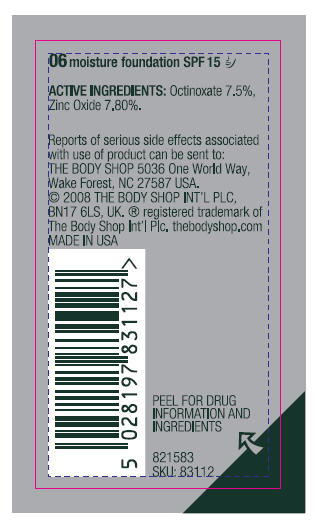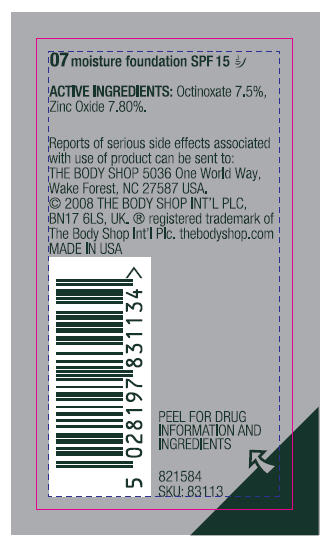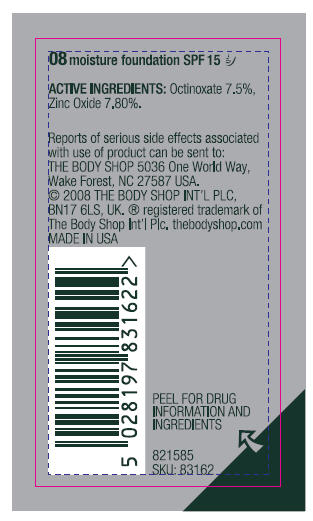 DRUG LABEL: 01 Moisture Foundation SPF 15
NDC: 57691-161 | Form: EMULSION
Manufacturer: The Body Shop Wake Forest
Category: otc | Type: HUMAN OTC DRUG LABEL
Date: 20100426

ACTIVE INGREDIENTS: Octinoxate 3.75 mg/0.5 mL; Zinc Oxide 3.9 mg/0.5 mL

moisture foundation SPF 15

Drug Facts

ACTIVE INGREDIENT

Active Ingredients | Purpose
Octinoxate (7.5%), | Sunscreen
Zinc Oxide (7.80%). | Sunscreen

Uses

- helps prevent sunburn.
- higher SPF gives more protection.

Warning

- For external use only.

When using this product

- keep out of eyes.

Rinse with water to remove.

Stop and ask a doctor if

- rash or irritation develops and lasts.

Keep out of reach of children

If swallowed, get medical help or contact a Poison Control Center right away.

Directions

- apply evenly before sun exposure and as needed.
- for use in children under 6 months old, ask a doctor.
- shake well before use.

Inactive Ingredients

Water, Cyclomethicone, Propylene Glycol Dicaprylate/Dicaprate, Caprylic/Capric Triglyceride, Dextrin Palmitate, Dimethicone, Cetyl PEG/PPG-10/1 Dimethicone, Isopropyl Lanolate, Sclerocarya Birrea (Marula) Oil, Phenoxyethanol, Polyethylene, Sodium Chloride, Beeswax, Boron Nitride, Ethylene Brassylate, Glycerin, Tocopheryl Acetate, Methylparaben, PEG-40 Hydrogenated Castor Oil, Hectorite, Phenyl Methicone, Xanthan Gum, Propylparaben, Triethoxycaprylylsilane, Sodium Hyaluronate, Pyrus Malus (Apple) Extract, Ethylparaben, Butylparaben, Isobutylparaben, Titanium Dioxide, Iron Oxides.

© 2008 THE BODY SHOP INT'L PLC, BN17 6LS, UK.

MADE IN USA DIST:THE BODY SHOP WAKE FOREST,
NC 27587, USA; ® registered trademark of
The Body Shop Int'l Plc. thebodyshop.com

PRINCIPAL DISPLAY PANEL - 30 mL label

THE BODY SHOP®

MOISTURE FOUNDATION
SPF 15
FOND DE TEINT HYDRATANT
IND 15

30 mL
(1.0 US FL OZ)

PRINCIPAL DISPLAY PANEL - 01 bottle label

01 moisture foundation SPF 15

ACTIVE INGREDIENTS: Octinoxate 7.5%,
Zinc Oxide 7.80%.

Reports of serious side effects associated
with use of product can be sent to:
THE BODY SHOP 5036 One World Way,
Wake Forest, NC 27587 USA.
© 2008 THE BODY SHOP INT'L PLC,
BN17 6LS, UK. ® registered trademark of
The Body Shop Int'l Plc. thebodyshop.com
MADE IN USA

PEEL FOR DRUG
INFORMATION AND
INGREDIENTS

821578
SKU: 83161

PRINCIPAL DISPLAY PANEL - 02 bottle label

02 moisture foundation SPF 15

ACTIVE INGREDIENTS: Octinoxate 7.5%,
Zinc Oxide 7.80%.

Reports of serious side effects associated
with use of product can be sent to:
THE BODY SHOP 5036 One World Way,
Wake Forest, NC 27587 USA.
© 2008 THE BODY SHOP INT'L PLC,
BN17 6LS, UK. ® registered trademark of
The Body Shop Int'l Plc. thebodyshop.com
MADE IN USA

PEEL FOR DRUG
INFORMATION AND
INGREDIENTS

821579
SKU: 83107

PRINCIPAL DISPLAY PANEL - 03 bottle label

03 moisture foundation SPF 15

ACTIVE INGREDIENTS: Octinoxate 7.5%,
Zinc Oxide 7.80%.

Reports of serious side effects associated
with use of product can be sent to:
THE BODY SHOP 5036 One World Way,
Wake Forest, NC 27587 USA.
© 2008 THE BODY SHOP INT'L PLC,
BN17 6LS, UK. ® registered trademark of
The Body Shop Int'l Plc. thebodyshop.com
MADE IN USA

PEEL FOR DRUG
INFORMATION AND
INGREDIENTS

821580
SKU: 83108

PRINCIPAL DISPLAY PANEL - 04 bottle label

04 moisture foundation SPF 15

ACTIVE INGREDIENTS: Octinoxate 7.5%,
Zinc Oxide 7.80%.

Reports of serious side effects associated
with use of product can be sent to:
THE BODY SHOP 5036 One World Way,
Wake Forest, NC 27587 USA.
© 2008 THE BODY SHOP INT'L PLC,
BN17 6LS, UK. ® registered trademark of
The Body Shop Int'l Plc. thebodyshop.com
MADE IN USA

PEEL FOR DRUG
INFORMATION AND
INGREDIENTS

821581
SKU: 83109

PRINCIPAL DISPLAY PANEL - 05 bottle label

05 moisture foundation SPF 15

ACTIVE INGREDIENTS: Octinoxate 7.5%,
Zinc Oxide 7.80%.

Reports of serious side effects associated
with use of product can be sent to:
THE BODY SHOP 5036 One World Way,
Wake Forest, NC 27587 USA.
© 2008 THE BODY SHOP INT'L PLC,
BN17 6LS, UK. ® registered trademark of
The Body Shop Int'l Plc. thebodyshop.com
MADE IN USA

PEEL FOR DRUG
INFORMATION AND
INGREDIENTS

821582
SKU: 83110

PRINCIPAL DISPLAY PANEL - 06 bottle label

06 moisture foundation SPF 15

ACTIVE INGREDIENTS: Octinoxate 7.5%,
Zinc Oxide 7.80%.

Reports of serious side effects associated
with use of product can be sent to:
THE BODY SHOP 5036 One World Way,
Wake Forest, NC 27587 USA.
© 2008 THE BODY SHOP INT'L PLC,
BN17 6LS, UK. ® registered trademark of
The Body Shop Int'l Plc. thebodyshop.com
MADE IN USA

PEEL FOR DRUG
INFORMATION AND
INGREDIENTS

821583
SKU: 83112

PRINCIPAL DISPLAY PANEL - 07 bottle label

07 moisture foundation SPF 15

ACTIVE INGREDIENTS: Octinoxate 7.5%,
Zinc Oxide 7.80%.

Reports of serious side effects associated
with use of product can be sent to:
THE BODY SHOP 5036 One World Way,
Wake Forest, NC 27587 USA.
© 2008 THE BODY SHOP INT'L PLC,
BN17 6LS, UK. ® registered trademark of
The Body Shop Int'l Plc. thebodyshop.com
MADE IN USA

PEEL FOR DRUG
INFORMATION AND
INGREDIENTS

821584
SKU: 83113

PRINCIPAL DISPLAY PANEL - 08 bottle label

08 moisture foundation SPF 15

ACTIVE INGREDIENTS: Octinoxate 7.5%,
Zinc Oxide 7.80%.

Reports of serious side effects associated
with use of product can be sent to:
THE BODY SHOP 5036 One World Way,
Wake Forest, NC 27587 USA.
© 2008 THE BODY SHOP INT'L PLC,
BN17 6LS, UK. ® registered trademark of
The Body Shop Int'l Plc. thebodyshop.com
MADE IN USA

PEEL FOR DRUG
INFORMATION AND
INGREDIENTS

821585
SKU: 83162